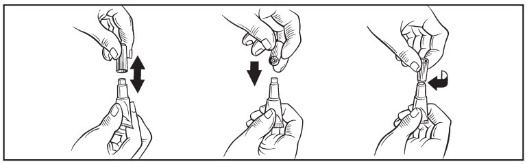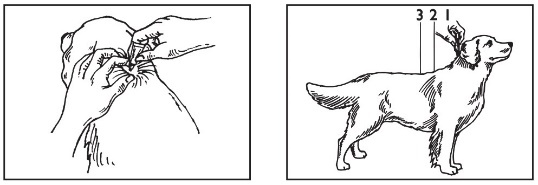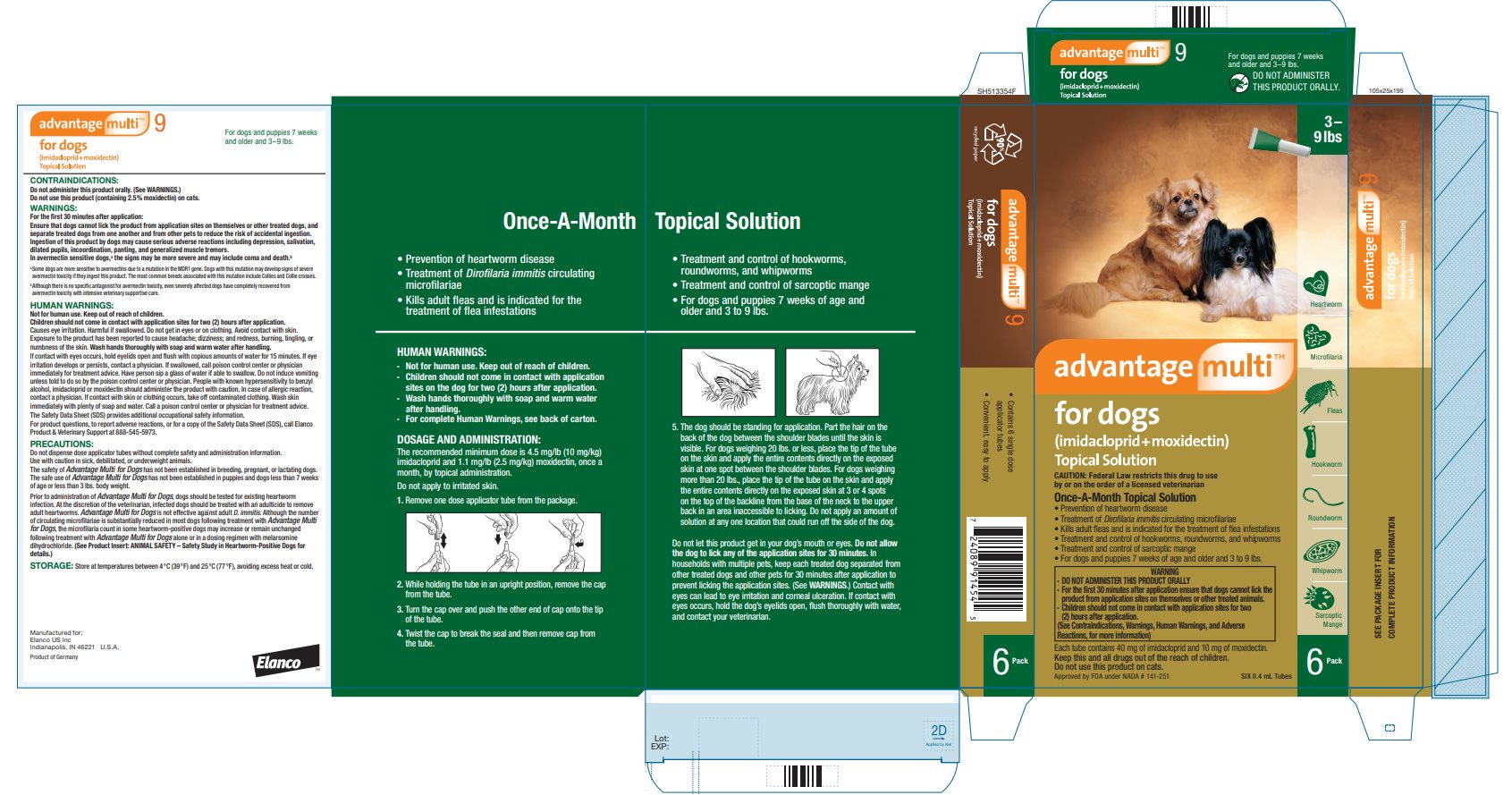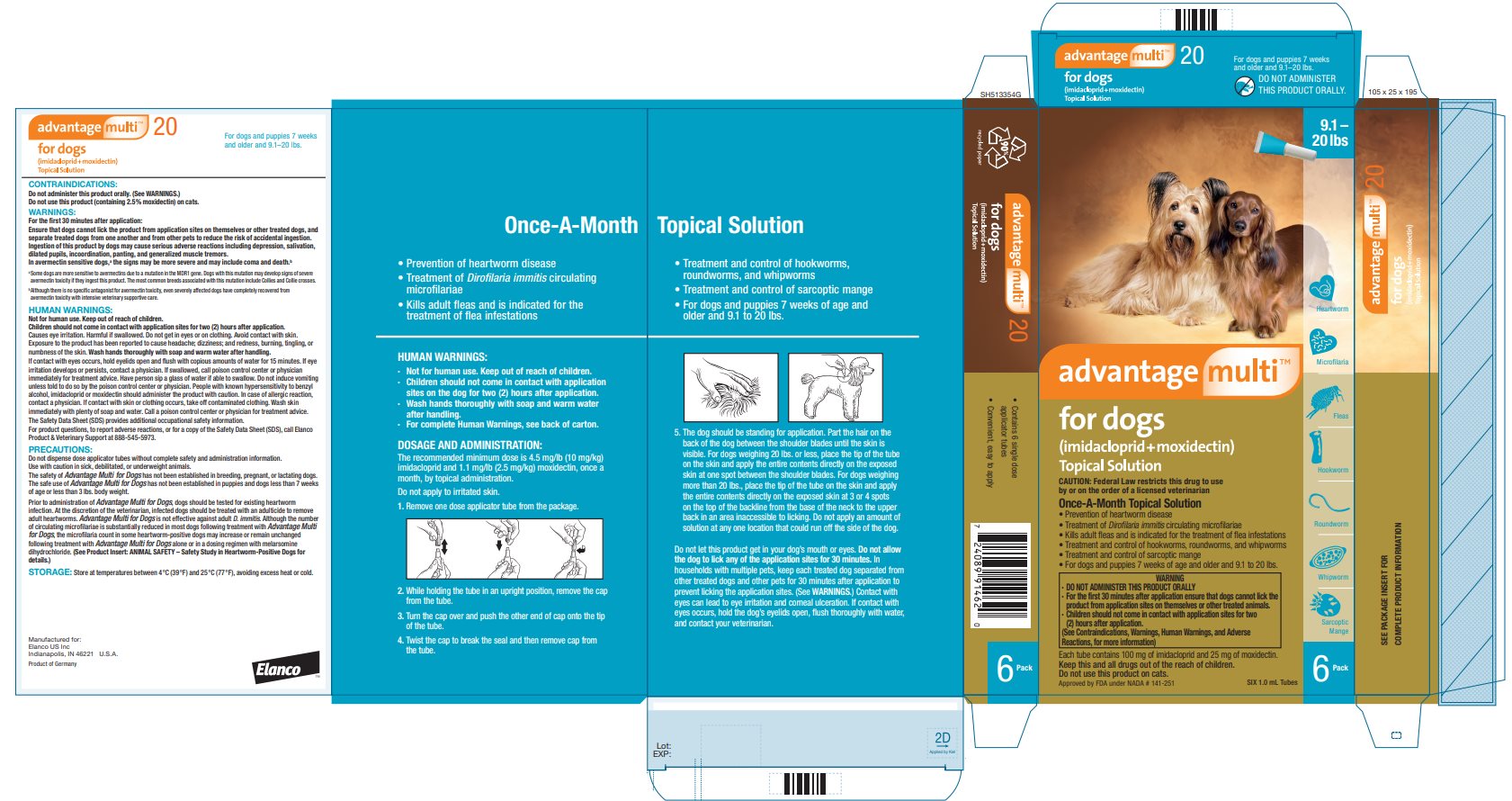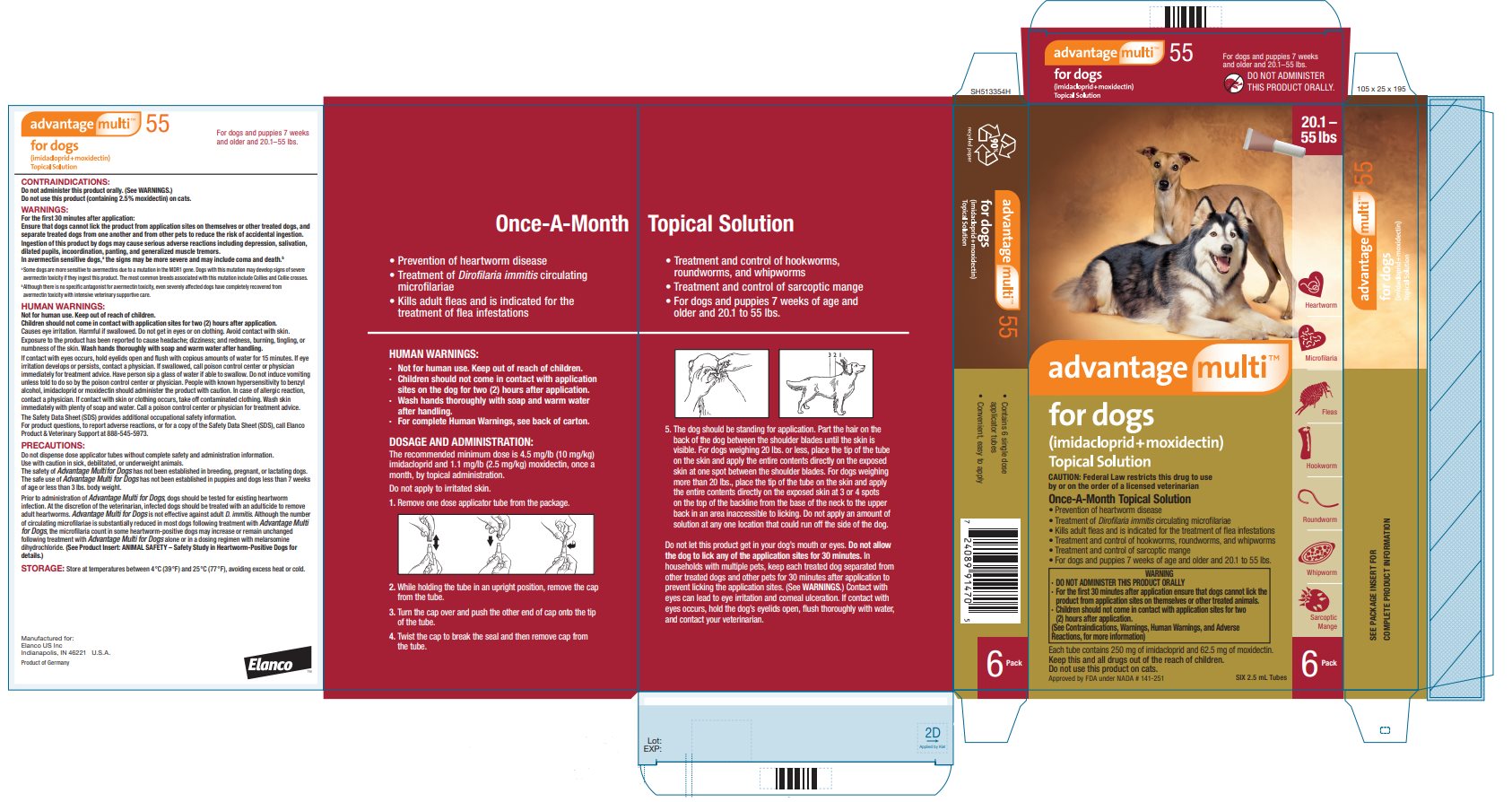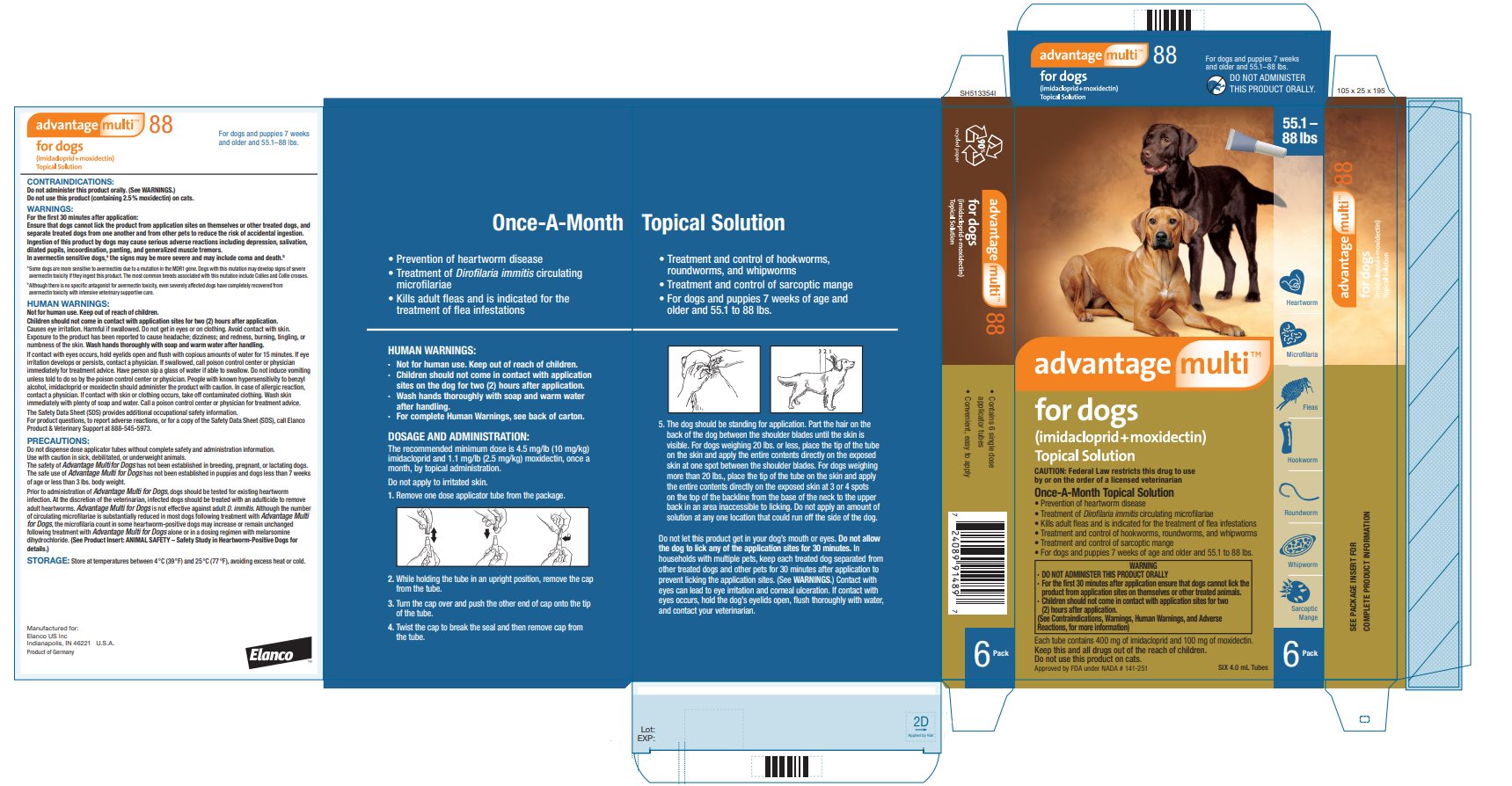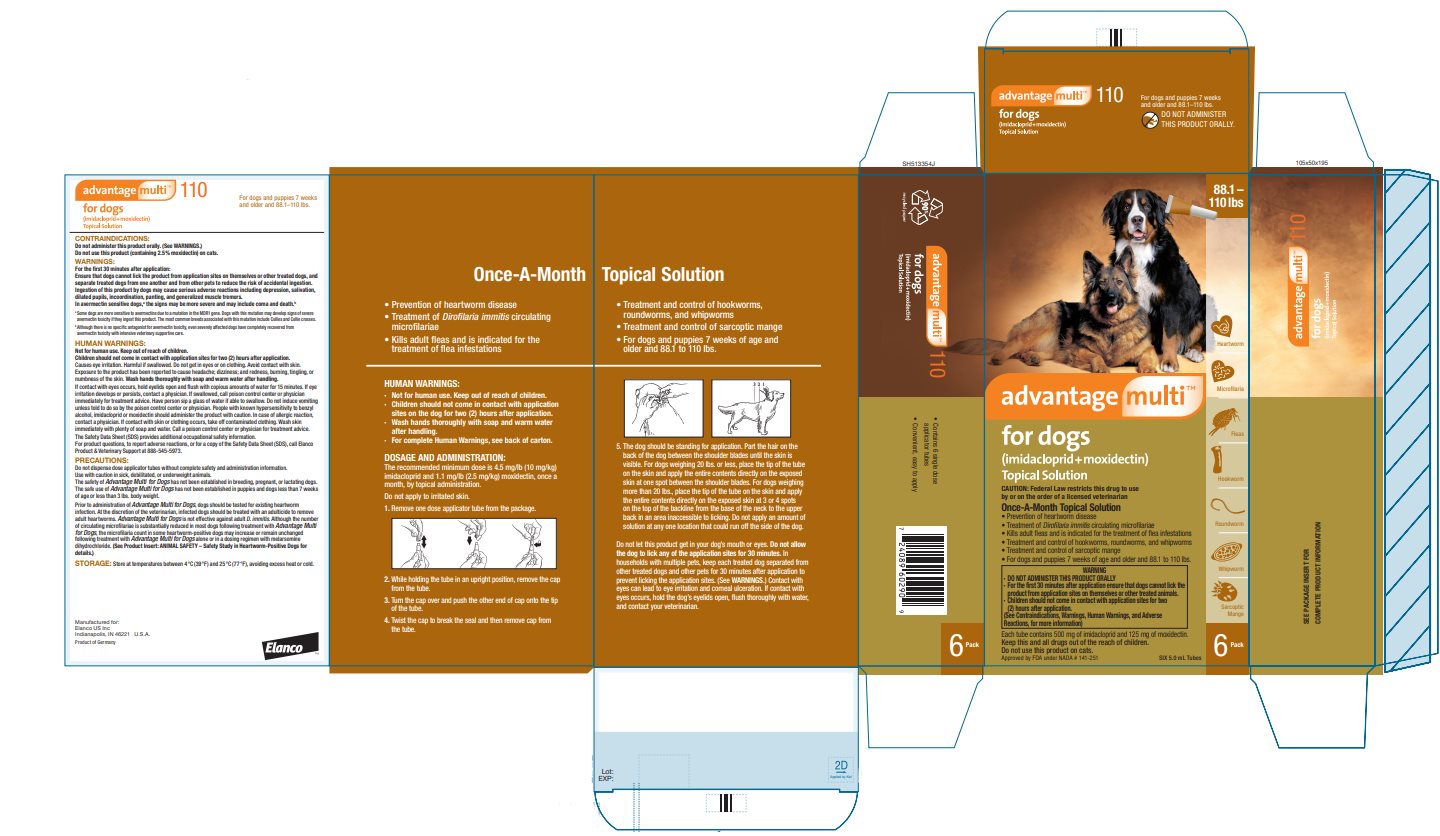 DRUG LABEL: ADVANTAGE MULTI FOR DOGS
NDC: 58198-0048 | Form: SOLUTION
Manufacturer: Elanco US Inc.
Category: animal | Type: PRESCRIPTION ANIMAL DRUG LABEL
Date: 20251029

ACTIVE INGREDIENTS: IMIDACLOPRID 100 mg/1 mL; MOXIDECTIN 25 mg/1 mL

ElancoTM
advantage multi™
for dogs
(imidacloprid+moxidectin)
Topical Solution

Once-a-month topical solution for the prevention of heartworm disease, the treatment of circulating microfilariae, kills adult fleas, is indicated for the treatment of flea infestations, the treatment and control of sarcoptic mange, as well as the treatment and control of intestinal parasite infections in dogs and puppies that are at least 7 weeks of age and that weigh at least 3 lbs.

WARNING

• DO NOT ADMINISTER THIS PRODUCT ORALLY

• For the first 30 minutes after application ensure that dogs cannot lick the product from application sites on themselves or other treated animals.

• Children should not come in contact with application sites for two (2) hours after application.

(See Contraindications, Warnings, Human Warnings, and Adverse Reactions, for more information)

CAUTION:

Federal Law restricts this drug to use by or on the order of a licensed veterinarian.

DESCRIPTION:

Advantage Multi for Dogs (10 % imidacloprid + 2.5 % moxidectin) is a colorless to yellow ready-to-use solution packaged in single dose applicator tubes for topical treatment of dogs. The formulation and dosage schedule are designed to provide a minimum of 4.5 mg/lb (10 mg/kg) imidacloprid and 1.1 mg/lb (2.5 mg/kg) moxidectin based on body weight.

Imidacloprid is a chloronicotinyl nitroguanidine insecticide. The chemical name for imidacloprid is 1-[(6-Chloro-3-pyridinyl)methyl]-N-nitro-2-imidazolidinimine. Moxidectin is a semisynthetic macrocyclic lactone endectocide derived from the actinomycete Streptomycetes cyaneogriseus noncyanogenus. The chemical name for moxidectin is [6R, 23E, 25S(E)]-5-0- Demethyl-28-deoxy-25-(1,3-dimethyl-1-butenyl)-6,28-epoxy-23-(methoxyimino) milbemycin B.

INDICATIONS:

Advantage Multi for Dogs is indicated for the prevention of heartworm disease caused by Dirofilaria immitis and the treatment of Dirofilaria immitis circulating microfilariae in heartworm-positive dogs. Advantage Multi for Dogs kills adult fleas and is indicated for the treatment of flea infestations (Ctenocephalides felis). Advantage Multi for Dogs is indicated for the treatment and control of sarcoptic mange caused by Sarcoptes scabiei var. canis. Advantage Multi for Dogs is also indicated for the treatment and control of the following intestinal parasites:

Intestinal Parasite |  | Intestinal Stage
Intestinal Parasite |  | Adult | Immature Adult | Fourth Stage Larvae
Hookworm Species | Ancylostoma caninum | X | X | X
Hookworm Species | Uncinaria stenocephala | X | X | X
Roundworm Species | Toxocara canis | X |  | X
Roundworm Species | Toxascaris leonina | X
Whipworm | Trichuris vulpis | X

DOSAGE AND ADMINISTRATION:

The recommended minimum dose is 4.5 mg/lb (10 mg/kg) imidacloprid and 1.1 mg/lb (2.5 mg/kg) moxidectin, once a month, by topical administration.

Do not apply to irritated skin.

1. Remove one dose applicator tube from the package. As specified in the following table, administer the entire contents of the Advantage Multi for Dogs tube that correctly corresponds with the body weight of the dog.

Dog (lbs.) | Advantage Multi For Dogs | Volume (mL) | Imidacloprid (mg) | Moxidectin (mg)
3–9 | Advantage Multi 9 | 0.4 | 40 | 10
9.1–20 | Advantage Multi 20 | 1.0 | 100 | 25
20.1–55 | Advantage Multi 55 | 2.5 | 250 | 62.5
55.1–88 | Advantage Multi 88 | 4.0 | 400 | 100
88.1–110* | Advantage Multi 110 | 5.0 | 500 | 125
* Dogs over 110 lbs. should be treated with the appropriate combination of Advantage Multi for Dogs tubes.

2. While holding the tube in an upright position, remove the cap from the tube.
3. Turn the cap over and push the other end of cap onto the tip of the tube.
4. Twist the cap to break the seal and then remove cap from the tube.
5. The dog should be standing for application. Part the hair on the back of the dog between the shoulder blades until the skin is visible. For dogs weighing 20 lbs. or less, place the tip of the tube on the skin and apply the entire contents directly on the exposed skin at one spot between the shoulder blades. For dogs weighing more than 20 lbs., place the tip of the tube on the skin and apply the entire contents directly on the exposed skin at 3 or 4 spots on the top of the backline from the base of the neck to the upper back in an area inaccessible to licking. Do not apply an amount of solution at any one location that could run off the side of the dog.

Do not let this product get in your dog's mouth or eyes. Do not allow the dog to lick any of the application sites for 30 minutes. In households with multiple pets, keep each treated dog separated from other treated dogs and other pets for 30 minutes after application to prevent licking the application sites. (See WARNINGS.) Contact with eyes can lead to eye irritation and corneal ulceration. If contact with eyes occurs, hold the dog’s eyelids open, flush thoroughly with water, and contact your veterinarian.

Stiff hair, a damp appearance of the hair, pink skin, or a slight powdery residue may be observed at the application site on some animals. This is temporary and does not affect the safety and effectiveness of the product.

Shampooing 90 minutes after treatment does not reduce the effectiveness of Advantage Multi for Dogs in the prevention of heartworm disease. Shampooing or water immersion 4 days after treatment will not reduce the effectiveness of Advantage Multi for Dogs in the treatment of flea infestations. However, shampooing as often as once weekly may reduce the effectiveness of the product against fleas.

Heartworm Prevention: For prevention of heartworm disease, Advantage Multi for Dogs should be administered at one-month intervals. Advantage Multi for Dogs may be administered year-round or at a minimum should start one month before the first expected exposure to mosquitoes and should continue at monthly intervals until one month after the last exposure to mosquitoes. If a dose is missed and a 30-day interval between doses is exceeded, administer Advantage Multi for Dogs immediately and resume the monthly dosing schedule. When replacing another heartworm preventative product in a heartworm prevention program, the first treatment with Advantage Multi for Dogs should be given within one month of the last dose of the former medication.

Treatment of Circulating Microfilaria: For the treatment of circulating D. immitis microfilaria in heartworm-positive dogs, Advantage Multi for Dogs should be administered at one-month intervals. Treatment with an approved adulticide therapy is recommended because Advantage Multi for Dogs is not effective for the treatment of adult D. immitis.

(See PRECAUTIONS.)

Flea Treatment: For the treatment of flea infestations, Advantage Multi for Dogs should be administered at one-month intervals. If the dog is already infested with fleas when the first dose of Advantage Multi for Dogs is administered, adult fleas on the dog will be killed. However, reinfestation from the emergence of pre-existing pupae in the environment may continue to occur for six weeks or longer after treatment is initiated. Dogs treated with imidacloprid, including those with pre-existing flea allergy dermatitis have shown clinical improvement as a direct result of elimination of fleas from the dog.

Treatment and Control of Intestinal Nematode Infections:

For the treatment and control of intestinal hookworm infections caused by Ancylostoma caninum and Uncinaria stenocephala (adults, immature adults and fourth stage larvae) and roundworm infections caused by Toxocara canis (adults and fourth stage larvae), and Toxascaris leonina (adults), and whipworm infections caused by Trichuris vulpis (adults), Advantage Multi for Dogs should be administered once as a single topical dose.

Treatment and Control of Sarcoptic Mange: For the treatment and control of sarcoptic mange caused by Sarcoptes scabiei var. canis, Advantage Multi for Dogs should be administered as a single topical dose. A second monthly dose may be administered if necessary.

CONTRAINDICATIONS:

Do not administer this product orally. (See WARNINGS.)

Do not use this product (containing 2.5 % moxidectin) on cats.

WARNINGS

For the first 30 minutes after application:

Ensure that dogs cannot lick the product from application sites on themselves or other treated dogs, and

Separate treated dogs from one another and from other pets to reduce the risk of accidental ingestion.

Ingestion of this product by dogs may cause serious adverse reactions including depression, salivation, dilated pupils, incoordination, panting, and generalized muscle tremors.

In avermectin sensitive dogs,a the signs may be more severe and may include coma and death.b

a Some dogs are more sensitive to avermectins due to a mutation in the MDR1 gene. Dogs with this mutation may develop signs of severe avermectin toxicity if they ingest this product. The most common breeds associated with this mutation include Collies and Collie crosses.

b Although there is no specific antagonist for avermectin toxicity, even severely affected dogs have completely recovered from avermectin toxicity with intensive veterinary supportive care.

HUMAN WARNINGS:

Not for human use. Keep out of the reach of children.

Children should not come in contact with application sites for two (2) hours after application.

Causes eye irritation. Harmful if swallowed. Do not get in eyes or on clothing. Avoid contact with skin. Exposure to the product has been reported to cause headache; dizziness; and redness, burning, tingling, or numbness of the skin. Wash hands thoroughly with soap and warm water after handling.

If contact with eyes occurs, hold eyelids open and flush with copious amounts of water for 15 minutes. If eye irritation develops or persists, contact a physician. If swallowed, call poison control center or physician immediately for treatment advice. Have person sip a glass of water if able to swallow. Do not induce vomiting unless told to do so by the poison control center or physician. People with known hypersensitivity to benzyl alcohol, imidacloprid or moxidectin should administer the product with caution. In case of allergic reaction, contact a physician. If contact with skin or clothing occurs, take off contaminated clothing. Wash skin immediately with plenty of soap and water. Call a poison control center or physician for treatment advice.

The Safety Data Sheet (SDS) provides additional occupational safety information. For product questions, to report adverse reactions, or for a copy of the Safety Data Sheet (SDS), call Elanco Product & Veterinary Support at 888-545-5973.

PRECAUTIONS:

Do not dispense dose applicator tubes without complete safety and administration information.

Use with caution in sick, debilitated, or underweight animals. The safety of Advantage Multi for Dogs has not been established in breeding, pregnant, or lactating dogs. The safe use of Advantage Multi for Dogs has not been established in puppies and dogs less than 7 weeks of age or less than 3 lbs. body weight.

Prior to administration of Advantage Multi for Dogs, dogs should be tested for existing heartworm infection. At the discretion of the veterinarian, infected dogs should be treated with an adulticide to remove adult heartworms. The safety of Advantage Multi for Dogs has not been evaluated when administered on the same day as an adulticide. Advantage Multi for Dogs is not effective against adult D. immitis. Although the number of circulating microfilariae is substantially reduced in most dogs following treatment with Advantage Multi for Dogs, the microfilaria count in some heartworm-positive dogs may increase or remain unchanged following treatment with Advantage Multi for Dogs alone or in a dosing regimen with melarsomine dihydrochloride.

(See ADVERSE REACTIONS and ANIMAL SAFETY – Safety Study in Heartworm-Positive Dogs.)

Advantage Multi for Dogs has not been evaluated in heartworm-positive dogs with Class 4 heartworm disease.

ADVERSE REACTIONS:

Heartworm-Negative Dogs

Field Studies: Following treatment with Advantage Multi for Dogs or an active control, dog owners reported the following post-treatment reactions:

OBSERVATION | Advantage Multi n = 128 | Active Control n = 68
Pruritus | 19 dogs (14.8 %) | 7 dogs (10.3 %)
Residue | 9 dogs (7.0 %) | 5 dogs (7.4 %)
Medicinal Odor | 5 dogs (3.9 %) | None observed
Lethargy | 1 dog (0.8 %) | 1 dog (1.5 %)
Inappetence | 1 dog (0.8 %) | 1 dog (1.5 %)
Hyperactivity | 1 dog (0.8 %) | None observed

During a field study using 61 dogs with pre-existing flea allergy dermatitis, one (1.6 %) dog experienced localized pruritus immediately after imidacloprid application, and one investigator noted hyperkeratosis at the application site of one dog (1.6 %).

In a field safety and effectiveness study, Advantage Multi for Dogs was administered to 92 client-owned dogs with sarcoptic mange. The dogs ranged in age from 2 months to 12.5 years and ranged in weight from 3 to 231.5 pounds. Adverse reactions in dogs treated with Advantage Multi for Dogs included hematochezia, diarrhea, vomiting, lethargy, inappetence, and pyoderma.

Laboratory Effectiveness Studies: One dog in a laboratory effectiveness study experienced weakness, depression, and unsteadiness between 6 and 9 days after application with Advantage Multi for Dogs. The signs resolved without intervention by day 10 post-application. The signs in this dog may have been related to peak serum levels of moxidectin, which vary between dogs, and occur between 1 and 21 days after application of Advantage Multi for Dogs.

The following clinical observations also occurred in laboratory effectiveness studies following application with Advantage Multi for Dogs and may be directly attributed to the drug or may be secondary to the intestinal parasite burden or other underlying conditions in the dogs: diarrhea, bloody stools, vomiting, anorexia, lethargy, coughing, ocular discharge and nasal discharge. Observations at the application sites included damp, stiff or greasy hair, the appearance of a white deposit on the hair, and mild erythema, which resolved without treatment within 2 to 48 hours.

Heartworm-Positive Dogs

Field Study: A 56-day field safety study was conducted in 214 D. immitis heartworm and microfilaria positive dogs with Class 1, 2 or 3 heartworm disease. All dogs received Advantage Multi for Dogs on Study Days 0 and 28; 108 dogs also received melarsomine dihydrochloride on Study Days – 14, 14, and 15. All dogs were hospitalized for a minimum of 12 hours following each treatment. Effectiveness against circulating D. immitis microfilariae was > 90 % at five of six sites; however, one site had an effectiveness of 73.3 %. The microfilaria count in some heartworm-positive dogs increased or remained unchanged following treatment with Advantage Multi for Dogs alone or in a dosing regimen with melarsomine dihydrochloride.

Following treatment with Advantage Multi for Dogs alone or in a dosing regimen with melarsomine dihydrochloride, the following adverse reactions were observed:

Adverse Reaction | Dogs Treated with Advantage Multi for Dogs Only n = 106 | Dogs Treated with Advantage Multi for Dogs + Melarsomine n = 108
Cough | 24 (22.6 %) | 25 (23.1 %)
Lethargy | 14 (13.2 %) | 42 (38.9 %)
Vomiting | 11 (10.4 %) | 18 (16.7 %)
Diarrhea, including hemorrhagic | 10 (9.4 %) | 22 (20.4 %)
Inappetence | 7 (6.6 %) | 19 (17.6 %)
Dyspnea | 6 (5.7 %) | 10 (9.3 %)
Tachypnea | 1 (< 1 %) | 7 (6.5 %)
Pulmonary Hemorrhage | 0 | 1 (< 1 %)
Death | 0 | 3 (2.8 %)

Three dogs treated with Advantage Multi for Dogs in a dosing regimen with melarsomine dihydrochloride died of pulmonary embolism from dead and dying heartworms. One dog, treated with Advantage Multi for Dogs and melarsomine dihydrochloride, experienced pulmonary hemorrhage and responded to supportive medical treatment. Following the first treatment with Advantage Multi for Dogs alone, two dogs experienced adverse reactions (coughing, vomiting, and dyspnea) that required hospitalization. In both groups, there were more adverse reactions to Advantage Multi for Dogs following the first treatment than the second treatment.

To report a suspected adverse reaction, call 888-545-5973.

Post-Approval Experience (2022)

The following adverse events are based on post-approval adverse drug experience reporting for Advantage Multi for Dogs. Not all adverse events are reported to FDA CVM. It is not always possible to reliably estimate the adverse event frequency or establish a causal relationship to product exposure using this data.

The following adverse events reported in dogs are listed in decreasing order of reporting frequency:
depression/lethargy, pruritus, vomiting, diarrhea, anorexia, application site reactions (alopecia, pruritus, erythema, and lesions, including blisters), hyperactivity, ataxia, trembling, seizures, panting, hypersalivation, anaphylaxis/anaphylactic reactions (hives, facial swelling, edema of the head), and corneal ulceration.

Serious reactions, including neurologic signs and death have been reported when cats have been exposed (orally and topically) to this product.

In humans, nausea, numbness or tingling of the mouth/lips and throat, ocular and dermal irritation, pruritus, headache, vomiting, diarrhea, depression and dyspnea have been reported following exposure to this product.

Contact Information:

For product questions, to report adverse drug experiences, or for a copy of the Safety Data Sheet (SDS), call Elanco Product & Veterinary Support at 888-545-5973.

For additional information about reporting adverse drug experiences for animal drugs, contact FDA at 1-888-FDA-VETS or http://www.fda.gov/reportanimalae.

ANIMAL SAFETY:

Heartworm-Negative Dogs

Field Study: In a controlled, double-masked, field safety study, Advantage Multi for Dogs was administered to 128 dogs of various breeds, 3 months to 15 years of age, weighing 4 to 157 pounds. Advantage Multi for Dogs was used safely in dogs concomitantly receiving ACE inhibitors, anticonvulsants, antihistamines, antimicrobials, chondroprotectants, corticosteroids, immunotherapeutics, MAO inhibitors, NSAIDs, ophthalmic medications, sympathomimetics, synthetic estrogens, thyroid hormones, and urinary acidifiers. Owners reported the following signs in their dogs after application of Advantage Multi for Dogs: pruritus, flaky/ greasy residue at the treatment site, medicinal odor, lethargy, inappetence, and hyperactivity.

(See ADVERSE REACTIONS.)

Safety Study in Puppies: Advantage Multi for Dogs was applied topically at 1, 3 and 5X the recommended dose to 7-week-old Beagle puppies once every 2 weeks for 6 treatments on days 0, 14, 28, 42, 56, and 70. Loose stools and diarrhea were observed in all groups, including the controls, throughout the study. Vomiting was seen in one puppy from the 1X treatment group (day 57), in two puppies from the 3X treatment group (days 1 and 79), and in one puppy from the 5X treatment group (day 1). Two puppies each in the 1X, 3X, and 5X groups had decreased appetites within 24 hours post-dosing. One puppy in the 1X treatment group had pruritus for one hour following the fifth treatment. A puppy from the 5X treatment group displayed rapid, difficult breathing from 4 to 8 hours following the second treatment.

Dermal Dose Tolerance Study: Advantage Multi for Dogs was administered topically to 8-month-old Beagle dogs at 10X the recommended dose once. One dog showed signs of treatment site irritation after application. Two dogs vomited, one at 6 hours and one at 6 days post-treatment. Increased RBC, hemoglobin, activated partial thromboplastin, and direct bilirubin were observed in the treated group. Dogs in the treated group did not gain as much weight as the control group.

Oral Safety Study in Beagles: Advantage Multi for Dogs was administered once orally at the recommended topical dose to 12 dogs. Six dogs vomited within 1 hour of receiving the test article, 2 of these dogs vomited again at 2 hours, and 1 dog vomited again up to 18 hours post-dosing. One dog exhibited shaking (nervousness) 1 hour post-dosing. Another dog exhibited abnormal neurological signs (circling, ataxia, generalized muscle tremors, and dilated pupils with a slow pupillary light response) starting at 4 hours post-dosing through 18 hours post-dosing. Without treatment, this dog was neurologically normal at 24 hours and had a normal appetite by 48 hours post-dosing.

(See CONTRAINDICATIONS.)

Dermal Safety Study in Ivermectin-Sensitive Collies:

Advantage Multi for Dogs was administered topically at 3 and 5X the recommended dose every 28 days for 3 treatments to Collies which had been prescreened for avermectin sensitivity. No clinical abnormalities were observed.

Oral Safety Study in Ivermectin-Sensitive Collies:

Advantage Multi for Dogs was administered orally to 5 pre-screened ivermectin-sensitive Collies. The Collies were asymptomatic after ingesting 10 % of the minimum labeled dose. At 40 % of the minimum recommended topical dose, 4 of the dogs experienced neurological signs indicative of avermectin toxicity including depression, ataxia, mydriasis, salivation, muscle fasciculation, and coma, and were euthanized.

(See CONTRAINDICATIONS.)

Heartworm-Positive Dogs

Laboratory Safety Study in Heartworm-Positive Dogs: Advantage Multi for Dogs was administered topically at 1 and 5X the recommended dose every 14 days for 3 treatments to dogs with adult heartworm infections and circulating microfilaria. At 5X, one dog was observed vomiting three hours after the second treatment. Hypersensitivity reactions were not seen in the 5X treatment group. Microfilaria counts decreased with treatment.

STORAGE INFORMATION:

Store at temperatures between 4 °C (39 °F) and 25 °C (77 °F), avoiding excess heat or cold.

HOW SUPPLIED:

Applications Per Package

6 x 0.4 mL tubes

6 x 1.0 mL tubes

6 x 2.5 mL tubes

6 x 4.0 mL tubes

6 x 5.0 mL tubes

Revised: August 2025

Approved by FDA under NADA # 141-251

Product of Germany

© 2025 Elanco or its affiliates.

Advantage Multi, Elanco and the diagonal bar logo are trademarks of Elanco or its affiliates.

ElancoTM

Manufactured for:
Elanco US Inc
Indianapolis, IN 46221 U.S.A.

PA513354X

Principal Display Panel - 0.4 mL Carton Label

3 –
9 lbs

Heartworm

Microfilaria

Fleas

Hookworm

Roundworm

Whipworm

Sarcoptic
Mange

6 Pack

advantage multi™
for dogs
(imidacloprid+moxidectin)
Topical Solution

CAUTION: Federal Law restricts this drug to use
by or on the order of a licensed veterinarian

Once-A-Month Topical Solution

- Prevention of heartworm disease
- Treatment of Dirofilaria immitis circulating microfilariae
- Kills adult fleas and is indicated for the treatment of flea infestations
- Treatment and control of hookworms, roundworms, and whipworms
- Treatment and control of sarcoptic mange
- For dogs and puppies 7 weeks of age and older and 3 to 9 lbs.

WARNING

- DO NOT ADMINISTER THIS PRODUCT ORALLY
- For the first 30 minutes after application ensure that dogs cannot lick the
  product from application sites on themselves or other treated animals.
- Children should not come in contact with application sites for two
  (2) hours after application.

(See Contraindications, Warnings, Human Warnings, and Adverse
Reactions, for more information)

Each tube contains 40 mg of imidacloprid and 10 mg of moxidectin.

Keep this and all drugs out of the reach of children.

Do not use this product on cats.

Approved by FDA under NADA # 141-251

SIX 0.4 mL Tubes

Principal Display Panel - 1.0 mL Carton Label

9.1 -
20 lbs.

Heartworm

Microfilaria

Fleas

Hookworm

Roundworm

Whipworm

Sarcoptic
Mange

6 Pack

advantage multi™
for dogs
(imidacloprid+moxidectin)
Topical Solution

CAUTION: Federal Law restricts this drug to use
by or on the order of a licensed veterinarian

Once-A-Month Topical Solution

- Prevention of heartworm disease
- Treatment of Dirofilaria immitis circulating microfilariae
- Kills adult fleas and is indicated for the treatment of flea infestations
- Treatment and control of hookworms, roundworms, and whipworms
- Treatment and control of sarcoptic mange
- For dogs and puppies 7 weeks of age and older and 9.1 to 20 lbs.

WARNING

- DO NOT ADMINISTER THIS PRODUCT ORALLY
- For the first 30 minutes after application ensure that dogs cannot lick the
  product from application sites on themselves or other treated animals.
- Children should not come in contact with application sites for two
  (2) hours after application.

(See Contraindications, Warnings, Human Warnings, and Adverse
Reactions, for more information)

Each tube contains 100 mg of imidacloprid and 25 mg of moxidectin.

Keep this and all drugs out of the reach of children.

Do not use this product on cats.

Approved by FDA under NADA # 141-251

SIX 1.0 mL Tubes

Principal Display Panel - 2.5 mL Carton Label

20.1 –
55 lbs

Heartworm

Microfilaria

Fleas

Hookworm

Roundworm

Whipworm

Sarcoptic
Mange

6 Pack

advantage multi™
for dogs
(imidacloprid+moxidectin)
Topical Solution

CAUTION: Federal Law restricts this drug to use
by or on the order of a licensed veterinarian

Once-A-Month Topical Solution

- Prevention of heartworm disease
- Treatment of Dirofilaria immitis circulating microfilariae
- Kills adult fleas and is indicated for the treatment of flea infestations
- Treatment and control of hookworms, roundworms, and whipworms
- Treatment and control of sarcoptic mange
- For dogs and puppies 7 weeks of age and older and 20.1 to 55 lbs.

WARNING

- DO NOT ADMINISTER THIS PRODUCT ORALLY
- For the first 30 minutes after application ensure that dogs cannot lick the
  product from application sites on themselves or other treated animals.
- Children should not come in contact with application sites for two
  (2) hours after application.

(See Contraindications, Warnings, Human Warnings, and Adverse
Reactions, for more information)

Each tube contains 250 mg of imidacloprid and 62.5 mg of moxidectin.

Keep this and all drugs out of the reach of children.

Do not use this product on cats.

Approved by FDA under NADA # 141-251

SIX 2.5 mL Tubes

Principal Display Panel - 4.0 mL Carton Label

55.1 –
88 lbs

Heartworm

Microfilaria

Fleas

Hookworm

Roundworm

Whipworm

Sarcoptic
Mange

6 Pack

advantage multi™
for dogs
(imidacloprid+moxidectin)
Topical Solution

CAUTION: Federal Law restricts this drug to use
by or on the order of a licensed veterinarian

Once-A-Month Topical Solution

- Prevention of heartworm disease
- Treatment of Dirofilaria immitis circulating microfilariae
- Kills adult fleas and is indicated for the treatment of flea infestations
- Treatment and control of hookworms, roundworms, and whipworms
- Treatment and control of sarcoptic mange
- For dogs and puppies 7 weeks of age and older and 55.1 to 88 lbs.

WARNING

- DO NOT ADMINISTER THIS PRODUCT ORALLY
- For the first 30 minutes after application ensure that dogs cannot lick the
  product from application sites on themselves or other treated animals.
- Children should not come in contact with application sites for two
  (2) hours after application.

(See Contraindications, Warnings, Human Warnings, and Adverse
Reactions, for more information)

Each tube contains 400 mg of imidacloprid and 100 mg of moxidectin.

Keep this and all drugs out of the reach of children.

Do not use this product on cats.

Approved by FDA under NADA # 141-251

SIX 4.0 mL Tubes

Principal Display Panel - 5.0 mL Carton Label

88.1 –
110 lbs

Heartworm

Microfilaria

Fleas

Hookworm

Roundworm

Whipworm

Sarcoptic
Mange

6 Pack

advantage multi™
for dogs
(imidacloprid+moxidectin)
Topical Solution

CAUTION: Federal Law restricts this drug to use
by or on the order of a licensed veterinarian

Once-A-Month Topical Solution

- Prevention of heartworm disease
- Treatment of Dirofilaria immitis circulating microfilariae
- Kills adult fleas and is indicated for the treatment of flea infestations
- Treatment and control of hookworms, roundworms, and whipworms
- Treatment and control of sarcoptic mange
- For dogs and puppies 7 weeks of age and older and 88.1 to 110 lbs.

WARNING

- DO NOT ADMINISTER THIS PRODUCT ORALLY
- For the first 30 minutes after application ensure that dogs cannot lick the
  product from application sites on themselves or other treated animals.
- Children should not come in contact with application sites for two
  (2) hours after application.

(See Contraindications, Warnings, Human Warnings, and Adverse
Reactions, for more information)

Each tube contains 500 mg of imidacloprid and 125 mg of moxidectin.

Keep this and all drugs out of the reach of children.

Do not use this product on cats.

Approved by FDA under NADA # 141-251

SIX 5.0 mL Tubes